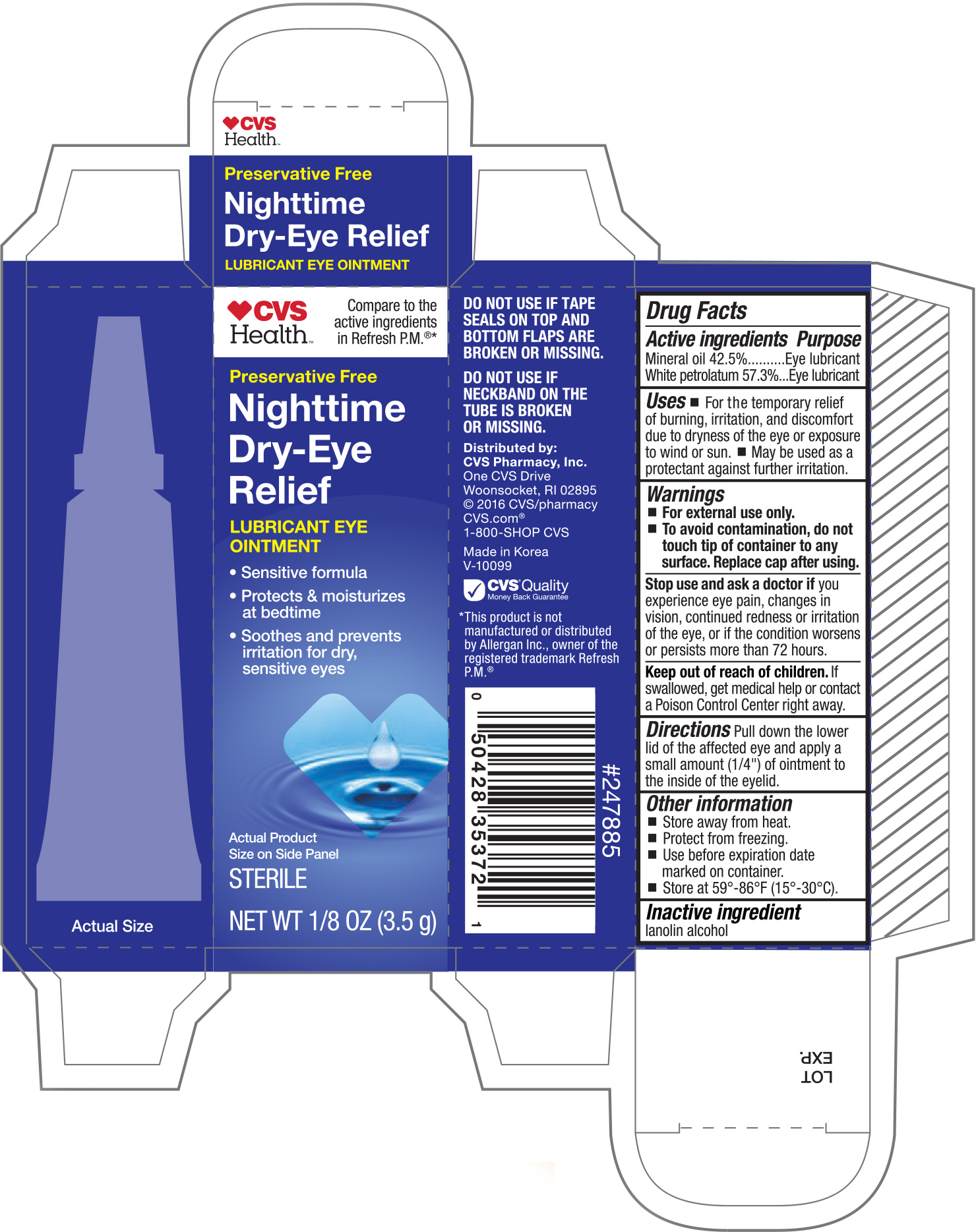 DRUG LABEL: CVS Nighttime Dry-Eye Relief
NDC: 59779-788 | Form: OINTMENT
Manufacturer: CVS Pharmacy, Inc.
Category: otc | Type: HUMAN OTC DRUG LABEL
Date: 20171127

ACTIVE INGREDIENTS: MINERAL OIL 425 mg/1 g; PETROLATUM 573 mg/1 g
INACTIVE INGREDIENTS: LANOLIN ALCOHOLS

CVS Nighttime Dry-Eye Relief 0.12oz(NBE Refresh PM)

Active ingredients Purpose

Mineral oil 42.5%............................Eye lubricant

White petrolatum 57.3%..................Eye lubricant

Uses

- For the temporary relief of burning, irritation, and discomfort due to dryness of the eye or exposure to wind or sun.
- May be used as a protectant against further irritation.

Warnings

- For external use only.
- To avoid contamination, do not touch tip of container to any surface. Replace cap after using.

Stop use and ask a doctor if you experience eye pain, changes in vision, continued redness or irritation of the eye, or if the condition worsens or persists more than 72 hours.

Keep out of reach of children.

If swallowed, get medical help or contact a Poison Control Center right away.

Directions

Pull down the lower lid of the affected eye and apply a small amount (1/4") of ointment to the inside of the eyelid.

Other information

- Store away from heat.
- Protect from freezing.
- Use before expiration date marked on container.
- Store at 59°-86°F (15°-30°C).

Inactive ingredient

lanolin alcohol

DOSAGE AND ADMINISTRATION

Distributed by:

CVS Pharmacy, Inc.

One CVS Drive

Woonsocket, RI 02895

©2016 CVS/pharmacy

CVS.com®

1-800-SHOP CVS

Made in Korea